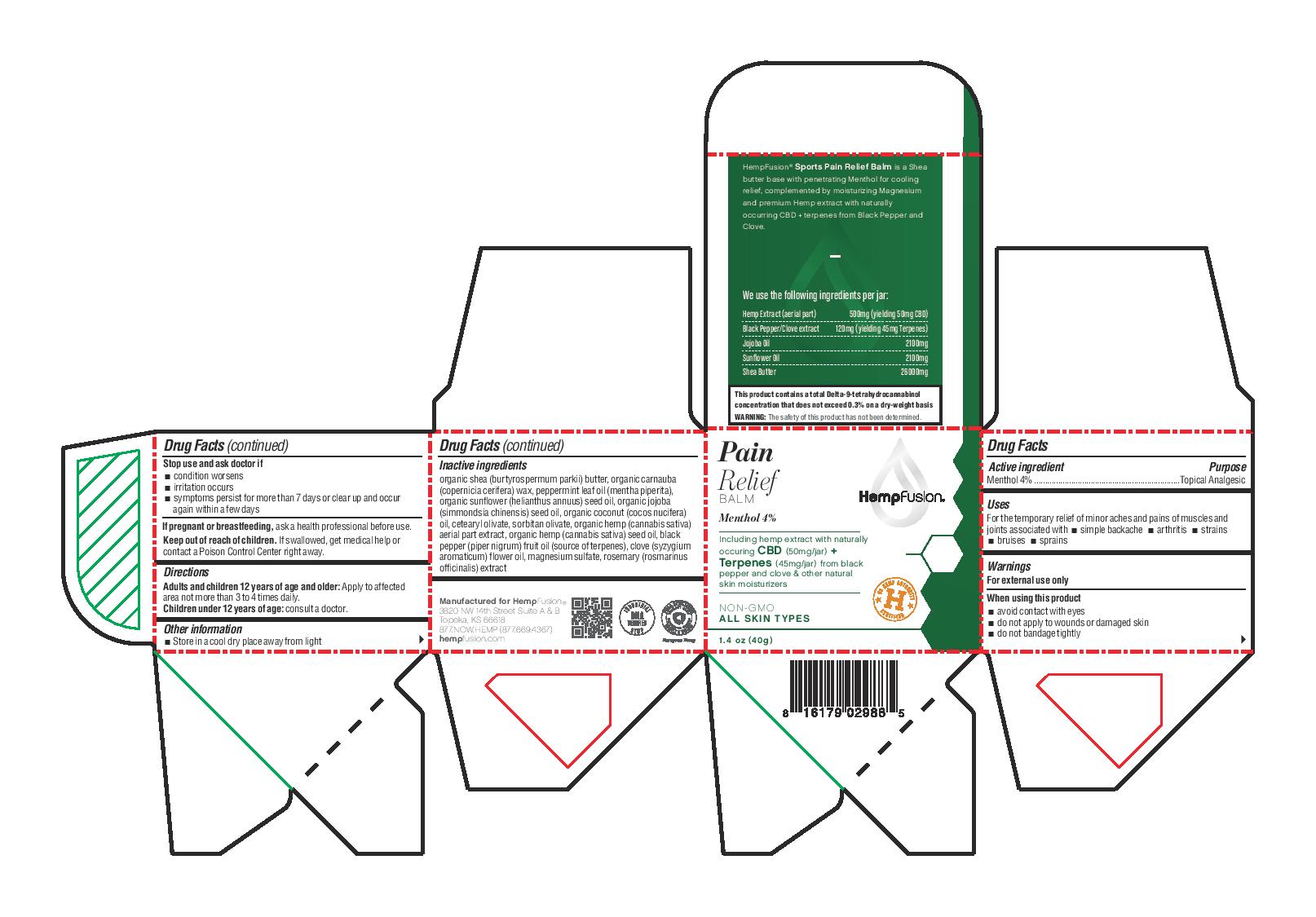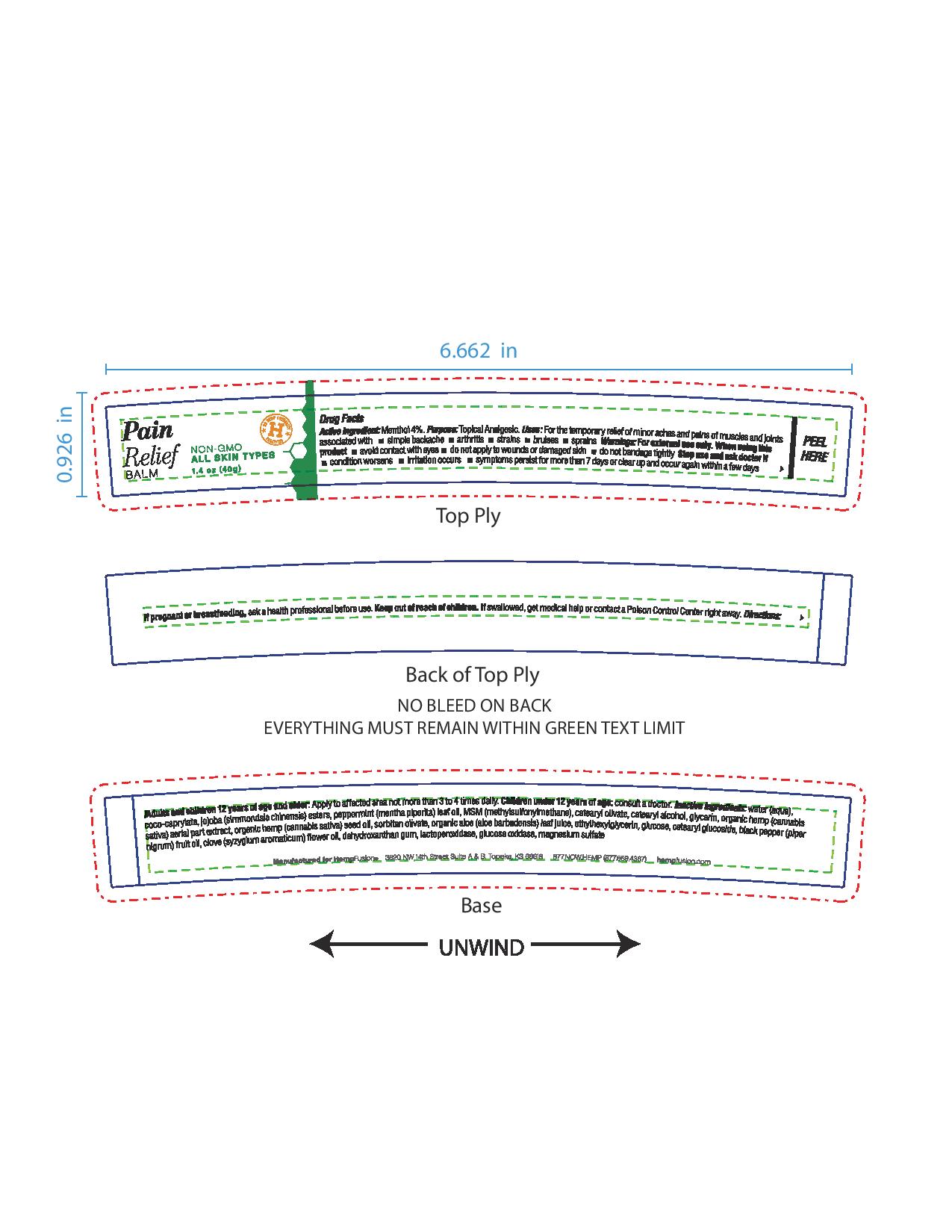 DRUG LABEL: Pain Relief Balm
NDC: 73672-988 | Form: CREAM
Manufacturer: HEMPFUSION, INC.
Category: otc | Type: HUMAN OTC DRUG LABEL
Date: 20210317

ACTIVE INGREDIENTS: MENTHOL 40 mg/1 g
INACTIVE INGREDIENTS: SUNFLOWER OIL; PEPPERMINT OIL; MAGNESIUM SULFATE, UNSPECIFIED FORM; ROSEMARY; CARNAUBA WAX; HEMP; BLACK PEPPER OIL; SHEA BUTTER; JOJOBA OIL; COCONUT OIL; CETEARYL OLIVATE; SORBITAN OLIVATE; CLOVE OIL

Pain Relief Balm

Active ingredient

Menthol 4%

Purpose

Menthol 4%...................Topical Analgesic

Uses

For the temporary relief of minor aches and pains of muslces and joints associated with

- simple backache
- arthritis
- strains
- bruises
- sprains

Warnings

For external use only

When using this product

- avoid contact with eyes
- do not apply to wounds or damaged skin
- do not bandage tightly

Stop use and ask doctor if

- condition worsens
- irritation occurs
- symptoms persist for more than 7 days or clear up and occur again within a few days

PREGNANCY OR BREAST FEEDING

If pregnant or breastfeeding, ask a health professional before use.

Keep out of reach of children. If swallowed, get medical help or contact a Poison Control Center right away.

Directions

Adults and children 12 years of age and older: Apply to affected area not more than 3 to 4 times daily.

Children under 12 years of age: consult a doctor.

Other information

- Store in a cool dry place away from light

Inactive ingredients

organic shea (burtyrospermum parkii) butter, organic carnauba (copernicia cerifera) wax, peppermint leaf oil (mentha piperita), organic sunflower (helianthus annuus) seed oil, organic jojoba (simmondsia chinensis) seed oil, organic coconut (cocos nucifera) oil, cetearyl olivate, sorbitan olivate, organic hemp (cannabis sativa) aerial part extract, organic hemp (cannabis sativa) seed oil, black pepper (piper nigrum) fruit oil (source of terpenes), clove (syzygium aromaticum) flower oil, magnesium sulfate, rosemary (rosmarinus officinalis) extract

QUESTIONS

Manufactured for HempFusion

3820 NW 14th Street Suite A & B

Topeka, KS 66618

877.NOW.HEMP (877.669.4367)

hempfusion.com

Principal Display Panel

Pain

Relief

BALM

HempFusion

Menthol 4%

Including hemp extract with naturally occurring CBD (50mg/jar) + Terpenes (45mg/jar) from black pepper and clove & other nautral skin moisturizers

NON-GMO

ALL SKIN TYPES

1.4 oz (40g)